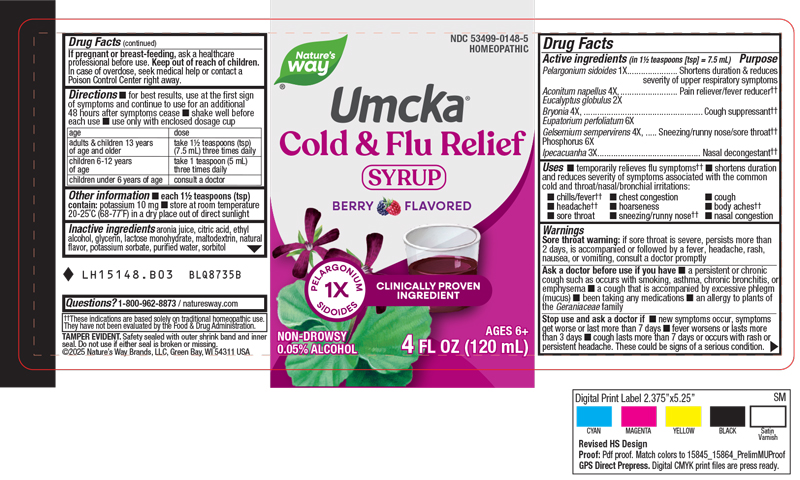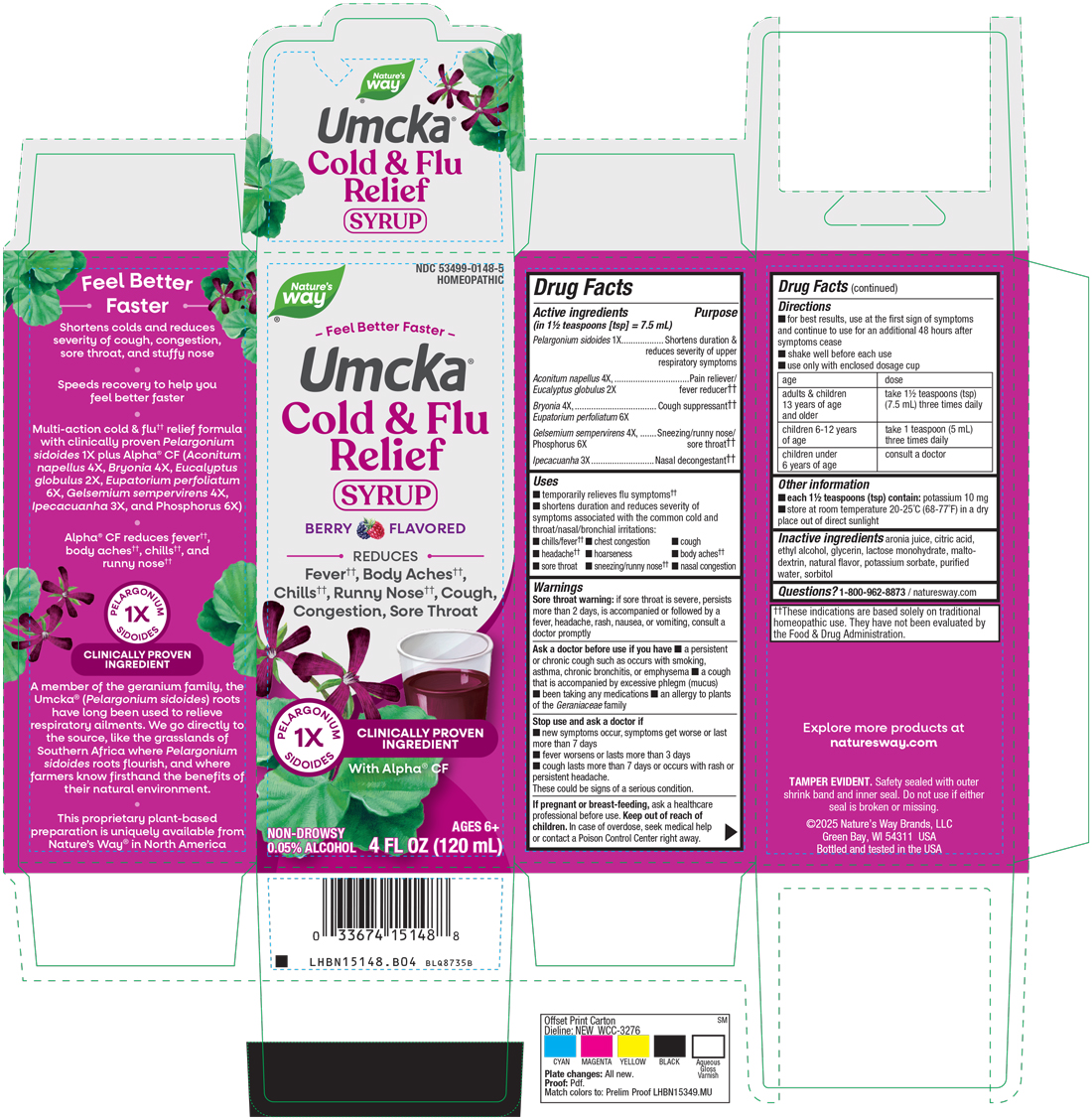 DRUG LABEL: Cold Flu Relief Berry
NDC: 53499-0148 | Form: SYRUP
Manufacturer: Schwabe North America
Category: homeopathic | Type: HUMAN OTC DRUG LABEL
Date: 20250910

ACTIVE INGREDIENTS: PELARGONIUM SIDOIDES ROOT 1 [hp_X]/120 mL; ACONITUM NAPELLUS 4 [hp_X]/120 mL; EUCALYPTUS GLOBULUS LEAF 2 [hp_X]/120 mL; BRYONIA ALBA ROOT 4 [hp_X]/120 mL; EUPATORIUM PERFOLIATUM FLOWERING TOP 6 [hp_X]/120 mL; GELSEMIUM SEMPERVIRENS ROOT 4 [hp_X]/120 mL; PHOSPHORUS 6 [hp_X]/120 mL; IPECAC 3 [hp_X]/120 mL
INACTIVE INGREDIENTS: ARONIA MELANOCARPA FRUIT JUICE; CITRIC ACID MONOHYDRATE; ALCOHOL; GLYCERIN; LACTOSE MONOHYDRATE; MALTODEXTRIN; WATER; SORBITOL; POTASSIUM SORBATE

Cold + Flu Relief Berry

Active Ingredients

Pelargonium sidoides 1X

Aconitum napellus 4X

Eucalyptus globulus 2X

Bryonia 4X

Eupatorium perfoliatum 6X

Gelsemium sempervirens 4X

Phosphorus 6X

Ipecacuanha 3X

Inactive Ingredient

Aronia Juice

Citric Acid

Ethyl Alcohol

Glycerin

Lactose Monohydrate

Maltodextrin

Natural Flavor

Potassium Sorbate

Purified Water

Sorbitol

Dosage & Administration

Directions

For best results, use at the first sign of symptoms and continue to use for an additional 48 hours after symptoms cease.

Shake well before each use.

Use only with enclosed dosage cup.

Adults & children 13 years of age and older: Take 1½ teaspoon (tsp) (7.5 mL) three times daily.

Children 6 to 12 years of age: Take 1 teaspoon (5 mL) three times daily.

Children under 6 years of age: consult a doctor.

Purpose

Temporarily relieves flu symptoms.

Shortens duration and reduces severity of symptoms associated with the common cold and throat/nasal/bronchial irritations: chills/fever, chest congestion, cough, headache, hoarseness, body aches, sore throat, sneezing/runny nose, nasal congestion.

Indications & Usage

Temporarily relieves flu symptoms.

Shortens duration and reduces severity of symptoms associated with the common cold and throat/nasal/bronchial irritations: chills/fever, chest congestion, cough, headache, hoarseness, body aches, sore throat, sneezing/runny nose, nasal congestion.

Warnings

Sore throat warning: if sore throat is severe, persists more than 2 days, is accompanied or followed by a fever, headache, rash, nausea, or vomiting, consult a doctor promptly.

Ask Doctor

Ask a doctor before use if you have a persistent or chronic cough such as occurs with smoking, asthma, chronic bronchitis, or emphysema, a cough that is accompanied by excessive phlegm (mucus), been taking any medications, an allergy to plants of the Geraniaceae family.

Stop Use

Stop use and ask a doctor if new symptoms occur, symptoms get worse or last more than 7 days, fever worsens or lasts more than 3 days, cough lasts more than 7 days or occurs with rash or persistent headache.

These could be signs of a serious condition.

Pregnancy or Breast Feeding

If pregnant or breast-feeding, ask a healthcare professional before use.

Keep out of reach of children

Overdose

In case of overdose, seek medical help or contact a Poison Control Center right away.